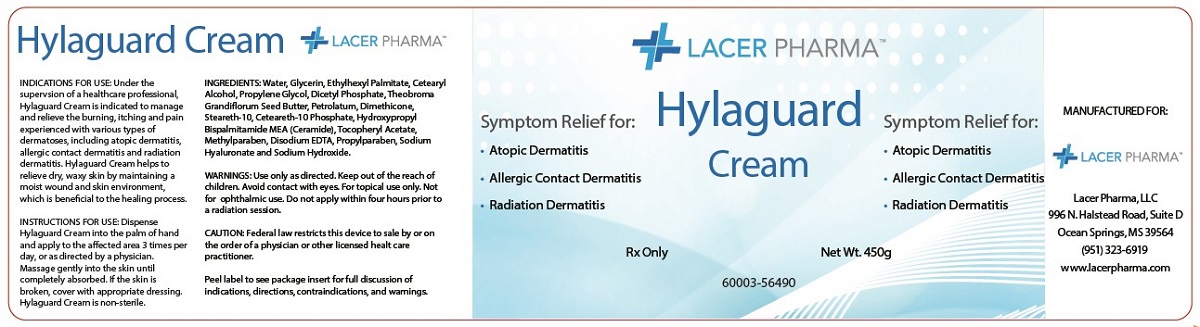 DRUG LABEL: Hylaguard Cream
NDC: 860003564905
Manufacturer: Lacer Pharma LLC
Category: other | Type: PRESCRIPTION MEDICAL DEVICE LABEL
Date: 20200430

Hylaguard Cream

Indications for Use

Under the supervision of a healthcare professional, Hylaguard Cream is indicated to manage and relieve the burning, itching and pain experienced with various types of dermatoses, including atopic dermatitis, allergic contact dermatitis and radiation dermatitis. Hylaguard Cream also helps to relieve dry, waxy skin by maintaining a moist wound and skin environment, which is beneficial to the healing process.

Device Description

Hylaguard Cream is a non-sterile, white to off-white, low odor, fragrance free, topical product. The Hylaguard Cream forms a physical barrier that helps to maintain a moist wound and skin environment. Hylaguard Cream is a prescription device.

Contraindications

Hylaguard Cream is contraindicated in persons with a known hypersensitivity to any of the components of the formulation.

Warnings

Use only as directed. Keep out of the reach of children. Avoid contact with eyes. For topical use only. Not for ophthalmic use. Do not apply within four hours prior to a radiation session.

Precautions and Observations

- Hylaguard Cream does not contain a sunscreen and should not be used prior to extended exposure to the sun.
- If clinical signs of infection are present, appropriate treatment should be initiated; use of Hylaguard Cream may be continued during the anti-infective therapy.
- If the condition does not improve within 10-14 days, consult a physician.
- Hylaguard Cream may dissolve fuchsin when this dye is used to define the margins of the radiation fields to be treated.

Instructions for Use

Dispense Hylaguard Cream into palm of hand and apply to affected area 3 times per day, or as directed by a physician. Massage gently into the skin until completely absorbed. If the skin is broken, cover with appropriate dressing. Hylaguard Cream is non-sterile.

Ingredients

Water, Glycerin, Ethylhexyl Palmitate, Cetearyl Alcohol, Propylene Glycol, Dicetyl Phosphate, Theobroma Grandiflorum Seed Butter, Petrolatum, Dimethicone, Steareth-10, Ceteareth-10 Phosphate, Hydroxypropyl Bispalmitamide MEA (Ceramide), Tocopheryl Acetate, Methylparaben, Disodium EDTA, Propylparaben, Sodium Hyaluronate and Sodium Hydroxide.

How Supplied

Hylaguard Cream is available in 450g commercial jars. 450g jar may be used for up to 60 days after opening.

CAUTION: Federal law restricts this device to sale by or on the order of a physician or other licensed health care practitioner.

Store between 59°F - 86°F (15°C - 30°C).